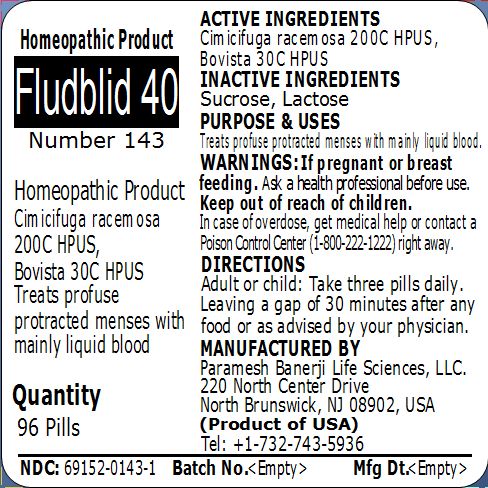 DRUG LABEL: Fludblid 40 (Number 143)
NDC: 69152-0143 | Form: PELLET
Manufacturer: Paramesh Banerji Life Sciences LLC
Category: homeopathic | Type: HUMAN OTC DRUG LABEL
Date: 20150307

ACTIVE INGREDIENTS: BLACK COHOSH 200 [hp_C]/1 1; LYCOPERDON UTRIFORME FRUITING BODY 30 [hp_C]/1 1
INACTIVE INGREDIENTS: SUCROSE; LACTOSE

Active Ingredients

Cimicifuga racemosa 200C HPUS, Bovista 30C HPUS

Inactive Ingredients

Sucrose, Lactose

Purpose

Treats profuse protracted menses with mainly liquid blood

Uses

Treats profuse protracted menses with mainly liquid blood

Warnings

If pregnant or breast feeding ask a health professional before use.

Keep out of reach of children. In case of overdose, get medical help or contact a Poison Control Center (1-800-222-1222) right away.

Direction

Adult or child: Take three pills daily. Leaving a gap of 30 minutes after any food or as advised by your physician.

Manufactured by

Paramesh Banerji Life Sciences, LLC

220 North Center Drive

North Brunswick, NJ 08902, USA

Product of USA

Tel: +1-732-743-5936

Principal Display Panel

Homeopathic Product

Fludblid 40

Number 143

Homeopathic Product

Cimicifuga racemosa 200C HPUS, Bovista 30C HPUS

Treats profuse protracted menses with mainly liquid blood

Quantity

96 Pills